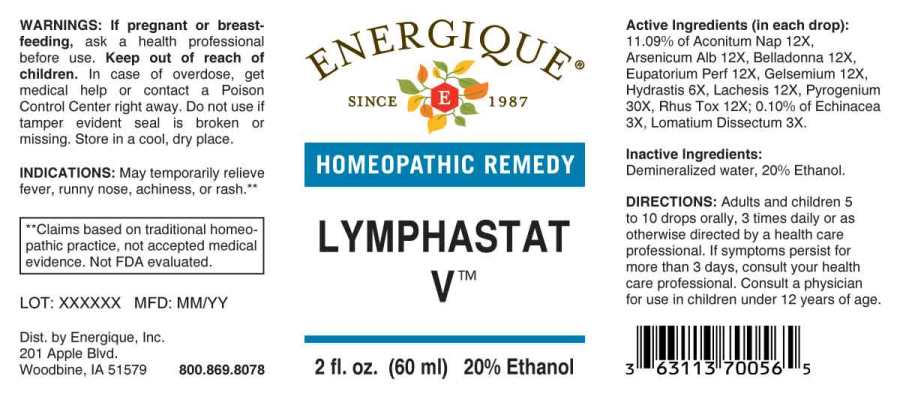 DRUG LABEL: LYMPHASTAT V
NDC: 44911-0622 | Form: LIQUID
Manufacturer: Energique, Inc.
Category: homeopathic | Type: HUMAN OTC DRUG LABEL
Date: 20240911

ACTIVE INGREDIENTS: ECHINACEA ANGUSTIFOLIA WHOLE 3 [hp_X]/1 mL; LOMATIUM DISSECTUM ROOT 3 [hp_X]/1 mL; GOLDENSEAL 6 [hp_X]/1 mL; ACONITUM NAPELLUS WHOLE 12 [hp_X]/1 mL; ARSENIC TRIOXIDE 12 [hp_X]/1 mL; ATROPA BELLADONNA 12 [hp_X]/1 mL; EUPATORIUM PERFOLIATUM FLOWERING TOP 12 [hp_X]/1 mL; GELSEMIUM SEMPERVIRENS ROOT 12 [hp_X]/1 mL; LACHESIS MUTA VENOM 12 [hp_X]/1 mL; TOXICODENDRON PUBESCENS LEAF 12 [hp_X]/1 mL
INACTIVE INGREDIENTS: WATER; ALCOHOL

Drug Facts:

ACTIVE INGREDIENTS:

(in each drop): 11.09% of Aconitum Napellus 12X, Arsenicum Album 12X, Belladonna 12X, Eupatorium Perfoliatum 12X, Gelsemium Sempervirens 12X, Hydrastis Canadensis 6X, Lachesis Mutus 12X, Pyrogenium 30X, Rhus Tox 12X; 0.10% of Echinacea (Angustifolia) 3X, Lomatium Dissectum 3X.

INDICATIONS:

May temporarily relieve symptoms associated with viral infections, such as fever, rash, and achiness.**

**Claims based on traditional homeopathic practice, not accepted medical evidence. Not FDA evaluated.

WARNINGS:

If pregnant or breast-feeding, ask a health professional before use.

Keep out of reach of children. In case of overdose, get medical help or contact a Poison Control Center right away.

Do not use if tamper evident seal is broken or missing. Store in a cool, dry place.

Keep out of reach of children. In case of overdose, get medical help or contact a Poison Control Center right away.

DIRECTIONS:

Adults and children 5 to 10 drops orally, 3 times daily or as otherwise directed by a health care professional. If symptoms persist for more than 3 days, consult your health care professional. Consult a physician for use in children under 12 years of age.

INDICATIONS:

May temporarily relieve symptoms associated with viral infections, such as fever, rash, and achiness.**

**Claims based on traditional homeopathic practice, not accepted medical evidence. Not FDA evaluated.

INACTIVE INGREDIENTS:

Demineralized water, 20% Ethanol.

QUESTIONS:

Dist. by Energique, Inc.

201 Apple Blvd.

Woodbine, IA 51579 800.869.8078

PACKAGE LABEL DISPLAY:

ENERGIQUE

SINCE 1987

HOMEOPATHIC REMEDY

LYMPHASTAT

2 fl. oz. (60 ml)